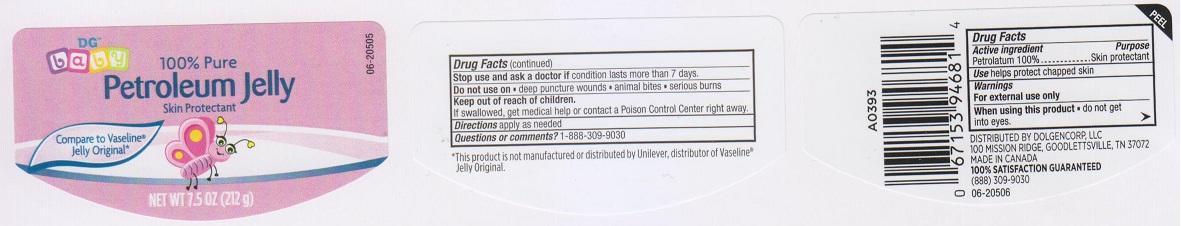 DRUG LABEL: DG BABY PETROLEUM
NDC: 55910-351 | Form: JELLY
Manufacturer: DOLGENCORP INC
Category: otc | Type: HUMAN OTC DRUG LABEL
Date: 20150819

ACTIVE INGREDIENTS: PETROLATUM 100 g/100 g

DRUG FACTS

Active ingredient

Petrolatum 100%

Purpose

Skin Protectant

Uses

helps protect chapped skin

Warnings

For external use only

When using this product

do not get into eyes

Stop use and ask a doctor if

condition lasts more than 7 days

Do not use on

- deep puncture wounds
- animal bites
- serious burns

Keep out of reach of children.

If swallowed, get medical help or contact a Poison Control Center right away.

Directions

apply as needed

Questions or comments?

1-888-309-9030